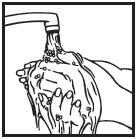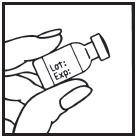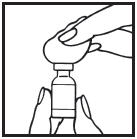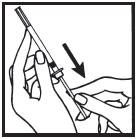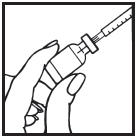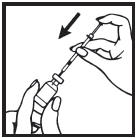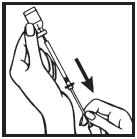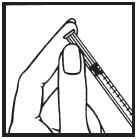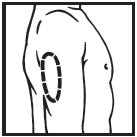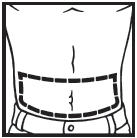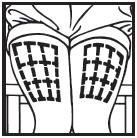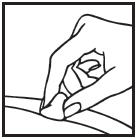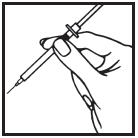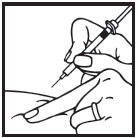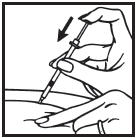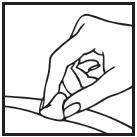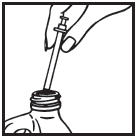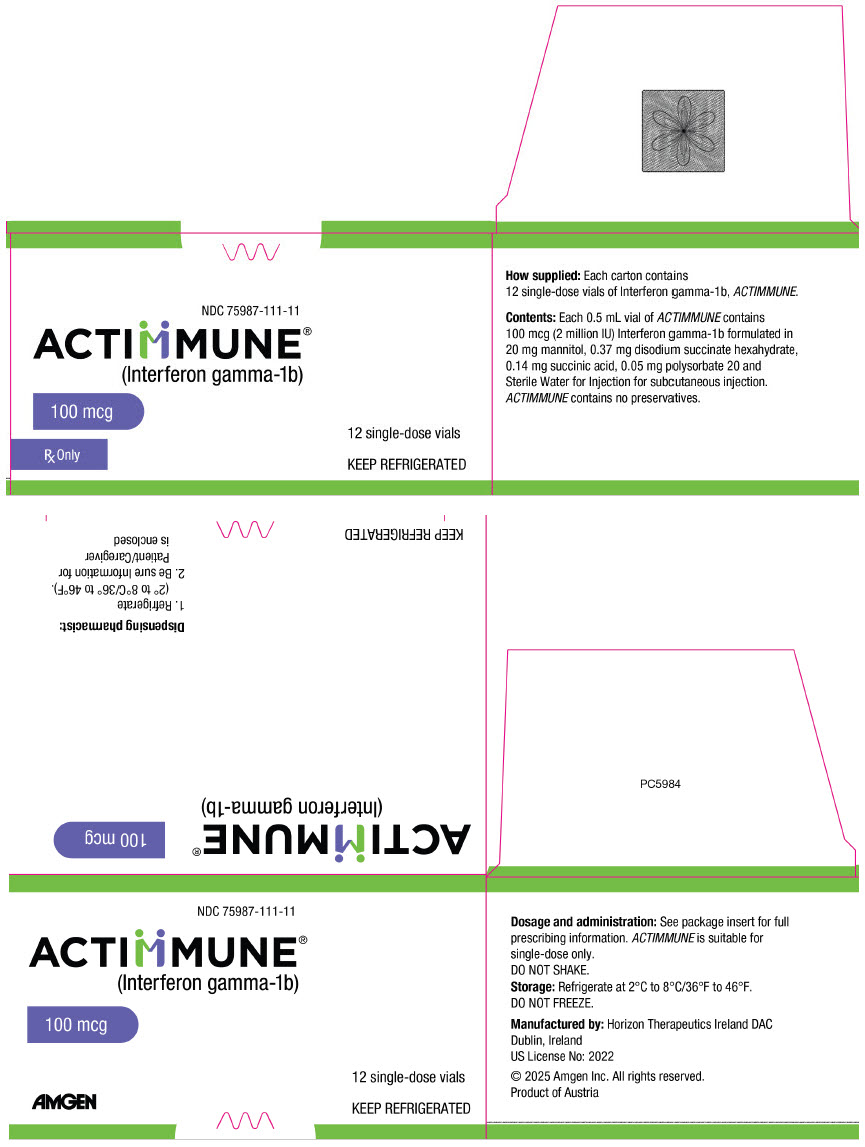 DRUG LABEL: ACTIMMUNE
NDC: 75987-111 | Form: INJECTION, SOLUTION
Manufacturer: Horizon Therapeutics USA, Inc.
Category: prescription | Type: HUMAN PRESCRIPTION DRUG LABEL
Date: 20250417

ACTIVE INGREDIENTS: INTERFERON GAMMA-1B 100 ug/0.5 mL
INACTIVE INGREDIENTS: MANNITOL 20 mg/0.5 mL; SODIUM SUCCINATE HEXAHYDRATE 0.37 mg/0.5 mL; SUCCINIC ACID; POLYSORBATE 20 0.05 mg/0.5 mL; WATER

HIGHLIGHTS OF PRESCRIBING INFORMATION

These highlights do not include all the information needed to use ACTIMMUNE® safely and effectively. See full prescribing information for ACTIMMUNE.
ACTIMMUNE® (interferon gamma-1b) injection, for subcutaneous use
Initial U.S. Approval: 1990

1 INDICATIONS AND USAGE

ACTIMMUNE is an interferon gamma indicated for:

- Reducing the frequency and severity of serious infections associated with Chronic Granulomatous Disease (CGD) (1)
- Delaying time to disease progression in patients with severe, malignant osteopetrosis (SMO) (1)

2 DOSAGE AND ADMINISTRATION

- For subcutaneous use only (2.1)
- The recommended dose is 50 mcg/m^2 for patients whose body surface area is greater than 0.5 m^2 and 1.5 mcg/kg/dose for patients whose body surface area is equal to or less than 0.5 m^2 three times weekly. (2.1)
- Monitor hematology, blood chemistries and urinalysis prior to the beginning of treatment and at 3-month intervals. (2.1)
- If severe reactions occur, reduce dose by 50 percent or discontinue therapy until the adverse reaction abates. (2.3)

3 DOSAGE FORMS AND STRENGTHS

Injection: 100 mcg (2 million International Units) of Interferon gamma-1b in 0.5 mL solution in a single dose vial. (3)

4 CONTRAINDICATIONS

Known hypersensitivity to interferon gamma, E. coli derived products, or any component of the product (4)

5 WARNINGS AND PRECAUTIONS

- Cardiovascular Disorders: Pre-existing cardiac conditions may be exacerbated. (5.1)
- Neurologic Disorders: Reduce dose or discontinue if decreased mental status, gait disturbance, dizziness occur. (5.2)
- Bone Marrow Toxicity: Monitor for neutropenia and thrombocytopenia particularly when administering ACTIMMUNE in combination with other potentially myelosuppressive agents. (5.3)
- Hepatic Toxicity: Reduce dose or discontinue to reverse severe elevations of aspartate transaminase (AST) and/or alanine transaminase (ALT); monitor liver function monthly in patients less than 1 year old. (5.4)
- Hypersensitivity Reactions: If serious hypersensitivity reactions occur, discontinue and institute appropriate medical therapy. (5.5)
- Renal Toxicity: Monitor renal function regularly when administering ACTIMMUNE to patients with severe renal insufficiency (5.6)

6 ADVERSE REACTIONS

Common adverse reactions (incidence rate 2% or greater) for ACTIMMUNE include fever, headache, rash, chills, injection site erythema or tenderness, fatigue, diarrhea. (6)
To report SUSPECTED ADVERSE REACTIONS, contact Amgen Inc.at 1 800 77 AMGEN (1 800 772 6436)or FDA at 1-800-FDA-1088 or www.fda.gov/medwatch.

7 DRUG INTERACTIONS

- Concomitant use of drugs with neurotoxic, hematotoxic or cardiotoxic effects may increase the toxicity of interferons. (7.2)
- Avoid simultaneous administration of ACTIMMUNE with other heterologous serum protein or immunological preparations (e.g., vaccines). (7.3)

8 USE IN SPECIFIC POPULATIONS

Based on animal data, may cause fetal harm. (8.1)

FULL PRESCRIBING INFORMATION

1 INDICATIONS AND USAGE

- ACTIMMUNE is indicated for reducing the frequency and severity of serious infections associated with Chronic Granulomatous Disease (CGD).
- ACTIMMUNE is indicated for delaying time to disease progression in patients with severe, malignant osteopetrosis (SMO).

2 DOSAGE AND ADMINISTRATION

2.1 Dosing Information

- The recommended dosage of ACTIMMUNE administered subcutaneously, for the treatment of patients with CGD and SMO is shown in Table 1 below:

Table 1: Recommended Dosage for ACTIMMUNE for the Treatment of Patients with CGD and SMO
Body Surface Area (m^2) | Dose (mcg/m^2) | Dose (International Units/m^2) [Note that the above activity is expressed in International Units (1 million International Units/50 mcg). This is equivalent to what was previously expressed as units (1.5 million units/50 mcg).] | Frequency
Greater than 0.5 m^2 | 50 mcg/m^2 | 1 million International Units/m^2 | Three times weekly (For example, Monday, Wednesday and Friday)
Equal to or less than 0.5 m^2 | 1.5 mcg/kg/dose | ------------ | Three times weekly (For example, Monday, Wednesday and Friday)

- Prior to the beginning of treatment and at three-month intervals during treatment the following laboratory tests are recommended for all patients on ACTIMMUNE (interferon gamma-1b) therapy [see Warnings and Precautions (5.3, 5.4, 5.6)]:
  - Hematologic tests – including complete blood counts, differential and platelet counts
  - Blood chemistries – including renal and liver function tests. In patients less than 1 year of age, liver function tests should be measured monthly [see Adverse Reactions (6.2)].
  - Urinalysis

2.2 Important Administration Instructions

- The optimum sites of subcutaneous injection are the right and left deltoid and anterior thigh.
- ACTIMMUNE can be administered by a physician, nurse, family member or patient when appropriately counseled in the administration of subcutaneous injections.
- Parenteral drug products should be inspected visually for particulate matter and discoloration prior to administration, whenever solution and container permit. ACTIMMUNE is a clear, colorless solution.
- ACTIMMUNE is for a single dose only. Discard any unused portion. ACTIMMUNE does not contain a preservative.
- ACTIMMUNE should not be mixed with other drugs in the same syringe.
- Administer ACTIMMUNE using either sterilized glass or plastic disposable syringes.

2.3 Dose Modification

- If severe reactions occur, the dosage should be reduced by 50 percent or therapy should be interrupted until the adverse reaction abates.
- Safety and efficacy has not been established for ACTIMMUNE given in doses greater or less than the recommended dose of 50 mcg/m^2. Higher doses (i.e., greater than 50 mcg/m^2) are not recommended. The minimum effective dose of ACTIMMUNE has not been established.

3 DOSAGE FORMS AND STRENGTHS

Injection: 100 mcg (2 million International Units) per 0.5 mL solution in a single-dose vial. ACTIMMUNE (interferon gamma-1b) is a sterile, clear, colorless solution filled in a single-dose vial for subcutaneous injection.

4 CONTRAINDICATIONS

ACTIMMUNE is contraindicated in patients who develop or have known hypersensitivity to interferon gamma, E. coli derived products, or any component of the product.

5 WARNINGS AND PRECAUTIONS

5.1 Cardiovascular Disorders

Acute and transient "flu-like" symptoms such as fever and chills induced by ACTIMMUNE at doses of 250 mcg/m^2/day (greater than 10 times the weekly recommended dose) or higher may exacerbate pre-existing cardiac conditions. Patients with pre-existing cardiac conditions, including ischemia, congestive heart failure or arrhythmia on ACTIMMUNE should be monitored for signs/symptoms of exacerbation. Some of the "flu-like" symptoms may be minimized by bedtime administration of ACTIMMUNE. Acetaminophen may also be used to ameliorate these effects.

5.2 Neurologic Disorders

Decreased mental status, gait disturbance and dizziness have been observed, particularly in patients receiving ACTIMMUNE doses greater than 250 mcg/m^2/day (greater than 10 times the weekly recommended dose). Most of these abnormalities were reversible within a few days upon dose reduction or discontinuation of therapy. Monitor patients when administering ACTIMMUNE to patients with seizure disorders or compromised central nervous system function.

5.3 Bone Marrow Toxicity

Reversible neutropenia and thrombocytopenia that can be severe and may be dose related have been observed during ACTIMMUNE therapy. Monitor neutrophil and platelet counts in patients with myelosuppression during treatment with ACTIMMUNE.

5.4 Hepatic Toxicity

Repeated administration of ACTIMMUNE to patients with advanced hepatic disease may result in accumulation of interferon gamma-1b. Frequent assessment of liver function in these patients is recommended.

Elevations of aspartate transaminase (AST) and/or alanine transaminase (ALT) (up to 25-fold) have been observed during ACTIMMUNE therapy. The incidence appeared to be higher in patients less than 1 year of age compared to older children. The transaminase elevations were reversible with reduction in dosage or interruption of ACTIMMUNE treatment. Patients begun on ACTIMMUNE before age one year should receive monthly assessments of liver function. If severe hepatic enzyme elevations develop, ACTIMMUNE dosage should be modified [see Dosage and Administration (2.3)].

5.5 Hypersensitivity Reactions

Isolated cases of acute serious hypersensitivity reactions have been observed in patients receiving ACTIMMUNE. If such an acute reaction develops the drug should be discontinued immediately and appropriate medical therapy instituted. Transient cutaneous rashes have occurred in some patients following injection of ACTIMMUNE that have necessitated treatment interruption.

5.6 Renal Toxicity

Monitor renal function regularly when administering ACTIMMUNE in patients with severe renal insufficiency because the possibility exists that with repeated administration, accumulation of interferon gamma-1b may occur. Renal toxicity has been reported in patients receiving ACTIMMUNE.

5.7 Allergic Reactions to Natural Rubber

The stopper of the glass vial for ACTIMMUNE contains natural rubber (a derivative of latex) which may cause allergic reactions.

6 ADVERSE REACTIONS

The following adverse reactions are described below and elsewhere in the warnings and precautions section of the labeling:

- Cardiovascular Disorders [see Warnings and Precautions (5.1)]
- Neurologic Disorders [see Warnings and Precautions (5.2)]
- Bone Marrow Toxicity [see Warnings and Precautions (5.3)]
- Hepatic Toxicity [see Warnings and Precautions (5.4)]
- Hypersensitivity Reactions [see Warnings and Precautions (5.5)]
- Renal Toxicity [see Warnings and Precautions (5.6)]

6.1 Clinical Trials Experience

Because clinical trials are conducted under widely varying conditions, adverse reaction rates observed in the clinical trials of a drug cannot be directly compared to rates in the clinical trials of another drug and may not reflect the rates observed in practice.

The following data on adverse reactions are based on the subcutaneous administration of ACTIMMUNE at a dose of 50 mcg/m^2, three times weekly, in patients with CGD during a clinical trial in the United States and Europe.

The most common adverse reactions observed in patients with CGD are shown in the following table:

Table 2: Adverse Reactions Occurring in 2% or Greater of CGD Patients Receiving ACTIMMUNE in Clinical Trials
Adverse Reactions | Percent of Patients
Adverse Reactions | ACTIMMUNE CGD (n=63) | Placebo CGD (n=65)
Fever | 52 | 28
Headache | 33 | 9
Rash | 17 | 6
Chills | 14 | 0
Injection site erythema or tenderness | 14 | 2
Fatigue | 14 | 11
Diarrhea | 14 | 12
Vomiting | 13 | 5
Nausea | 10 | 2
Myalgia | 6 | 0
Arthralgia | 2 | 0

Similar safety data were observed in 34 patients with SMO.

The clinical and laboratory toxicity associated with multiple dose studies of ACTIMMUNE is dose, route and schedule-dependent.

The most common adverse reactions include constitutional symptoms such as fever, headache, chills, myalgia or fatigue which may decrease in severity as treatment continues.

Less Common Adverse Reactions

The following adverse reactions are assessed as potentially related to ACTIMMUNE (interferon gamma-1b) therapy:

Blood and Lymphatic System — neutropenia (reversible), febrile neutropenia, leukopenia, and thrombocytopenia.

Cardiovascular — angina pectoris, arrhythmia, atrial fibrillation, atrioventricular block, cardiac failure (including congestive cardiac failure), tachyarrhythmia, heart block, (acute) myocardial infarction, myocardial ischemia, syncope, and tachycardia.

Gastrointestinal — abdominal pain, dyspepsia, gastrointestinal bleeding, granulomatous colitis, hepatic insufficiency, and pancreatitis, including pancreatitis with fatal outcome.

General Disorders and Administration Site Conditions — asthenia, chest pain/discomfort, influenza-like illness/flu-like symptoms, injection site hemorrhage, injection site pain, malaise, rigors, and weakness.

Hepatobiliary Disorders — hepatic insufficiency and hepatomegaly.

Immunological — hypersensitivity, increased autoantibodies, lupus-like syndrome (including systemic lupus erythematosus-flares and drug-induced lupus erythematosus), and Stevens-Johnson syndrome.

Infections and Infestations — upper respiratory tract infection.

Investigations — blood alkaline phosphatase increased, liver function tests abnormal/elevation of hepatic enzymes, increased triglycerides, and weight decreased.

Metabolic — hyponatremia, hypokalemia, hyperglycemia, and hypertriglyceridemia.

Musculoskeletal — back pain, clubbing, and muscle spasms.

Nervous System — dizziness (excluding vertigo), gait disturbance, headache, Parkinsonian symptoms, convulsion/seizure (including grand mal convulsions), and transient ischemic attacks.

Psychiatric — confusion, depression, disorientation, hallucinations, mental status changes, and mental status decreased.

Pulmonary — tachypnea, bronchospasm, pulmonary edema, and interstitial pneumonitis.

Renal — acute renal failure (which may be reversible) and proteinuria.

Skin and Subcutaneous Tissue Disorders — atopic dermatitis, (exacerbation of) dermatomyositis, transient cutaneous rash, and urticaria.

Vascular Disorder — deep venous thrombosis, hypotension, pulmonary embolism.

Abnormal Laboratory Test Values: Elevations of ALT and AST have been observed [see Warnings and Precautions (5.4)].

6.2 Postmarketing Experience

The following adverse reactions have been identified during post approval use of ACTIMMUNE. Because these reactions are reported voluntarily from a population of uncertain size, it is not always possible to reliably estimate their frequency or establish a causal relationship to drug exposure.

Children with CGD less than 3 years of age:

Data on the safety and activity of ACTIMMUNE in 37 patients under the age of 3 years was pooled from four uncontrolled postmarketing studies. The rate of serious infections per patient-year in this uncontrolled group was similar to the rate observed in the ACTIMMUNE treatment groups in controlled trials. Developmental parameters (height, weight and endocrine maturation) for this uncontrolled group conformed to national normative scales before and during ACTIMMUNE therapy.

In 6 of the 10 patients receiving ACTIMMUNE therapy before age one year 2-fold to 25-fold elevations from baseline of AST and/or ALT were observed. These elevations occurred as early as 7 days after starting treatment. Treatment with ACTIMMUNE was interrupted in all 6 of these patients and was restarted at a reduced dosage in 4. Liver transaminase values returned to baseline in all patients and transaminase elevation recurred in one patient upon ACTIMMUNE rechallenge. An 11-fold alkaline phosphatase elevation and hypokalemia in one patient and neutropenia (ANC = 525 cells/mm^3) in another patient resolved with interruption of ACTIMMUNE treatment and did not recur with rechallenge.

In the postmarketing safety database clinically significant adverse reactions observed during ACTIMMUNE therapy in children under the age of three years (n=14) included: two cases of hepatomegaly, and one case each of Stevens-Johnson syndrome, granulomatous colitis, urticaria, and atopic dermatitis.

6.3 Immunogenicity

As with all therapeutic proteins, there is a potential for immunogenicity. In clinical trials, 8 out of 33 ACTIMMUNE-treated patients developed non-neutralizing antibodies to interferon gamma-1b. No neutralizing antibodies to ACTIMMUNE have been detected in patients. In a Phase 1 study, none of the 38 ACTIMMUNE-treated healthy volunteers developed non-neutralizing antibodies to interferon gamma-1b.

The detection of antibody formation, including neutralizing antibody, in an assay may be influenced by several factors including assay methodology, sample handling, timing of sample collection, concomitant medications, and underlying disease. For these reasons, comparison of the incidence of antibodies to ACTIMMUNE with the incidence of antibodies to other products may be misleading.

7 DRUG INTERACTIONS

7.1 Myelosuppressive Agents

When administering ACTIMMUNE in combination with other potentially myelosuppressive agents, monitor neutrophil and platelet counts [see Warnings and Precautions (5.3)].

7.2 Drugs with Neurotoxic, Hematoxic or Cardiotoxic Effects

The concurrent use of drugs having neurotoxic (including effects on the central nervous system), hematotoxic, or cardiotoxic effects may increase the toxicity of interferons in these systems. It is theoretically possible that hepatotoxic and/or nephrotoxic drugs might have an effect on the clearance of ACTIMMUNE.

7.3 Immunological Preparations

Simultaneous administration of ACTIMMUNE with other heterologous serum protein preparations or immunological preparations (e.g., vaccines) should be avoided due to the risk of an unexpected, or amplified, immune response.

7.4 Effects on Cytochrome P-450 Pathways

Preclinical studies in rodents using species-specific interferon gamma have demonstrated a decrease in hepatic microsomal cytochrome P-450 concentrations. This could potentially lead to a depression of the hepatic metabolism of certain drugs that utilize this degradative pathway.

8 USE IN SPECIFIC POPULATIONS

8.1 Pregnancy

Risk Summary

There are no adequate and well-controlled studies in pregnant women. ACTIMMUNE should be used during pregnancy only if the potential benefit justifies the potential risk to the fetus.

Animal Data

ACTIMMUNE has shown an increased incidence of abortions in primates when given from gestation day 20 to 80 in doses approximately 100 times the human dose. A study in pregnant primates treated with subcutaneous doses 2 – 100 times the human dose failed to demonstrate teratogenic activity for ACTIMMUNE.

Female mice treated subcutaneously with recombinant murine IFN-interferon gamma (rmuIFN-gamma) at 280 times the maximum recommended clinical dose of ACTIMMUNE from shortly after birth through puberty but not during pregnancy had offspring which exhibited decreased body weight during the lactation period. The clinical significance of this finding observed following treatment of mice with rmuIFN-gamma is uncertain. For lower doses, there is no evidence of maternal toxicity, embryotoxicity, fetotoxicity or teratogenicity in preclinical studies.

8.2 Lactation

Risk Summary

It is not known whether ACTIMMUNE is excreted in human milk. Because many drugs are excreted in human milk and because of the potential for serious adverse reactions in nursing infants from ACTIMMUNE, a decision should be made whether to discontinue nursing or to discontinue the drug, dependent upon the importance of the drug to the mother.

8.3 Females and Males of Reproductive Potential

Infertility

Based on the information available, it cannot be excluded that the presence of higher levels of interferon gamma may impair male fertility and that in certain cases of female infertility increased levels of interferon gamma may have played a role [see Nonclinical Toxicology (13.1)].

In younger patients, the long-term effect on fertility is also not known.

8.4 Pediatric Use

The safety and effectiveness of ACTIMMUNE has been established in pediatric patients aged 1 year and older in CGD patients and 1 month and older in SMO patients [see Clinical Studies (14)]. There are no data available for pediatric patients below the age of 1 month.

8.5 Geriatric Use

Clinical studies of ACTIMMUNE did not include sufficient numbers of subjects aged 65 and over to determine whether they respond differently from younger subjects. In general, dose selection for an elderly patient should be cautious, usually starting at the low end of the dosing range, reflecting the greater frequency of decreased hepatic, renal, or cardiac function, and of concomitant disease or other drug therapy.

10 OVERDOSAGE

Central nervous system adverse reactions including decreased mental status, gait disturbance and dizziness have been observed, particularly in patients receiving doses greater than 100 mcg/m^2/day by intravenous or intramuscular administration. These abnormalities were reversible within a few days upon dose reduction or discontinuation of therapy. Reversible neutropenia, elevation of hepatic enzymes and of triglycerides, and thrombocytopenia have also been observed.

11 DESCRIPTION

ACTIMMUNE (Interferon gamma-1b), an interferon gamma, is a single-chain polypeptide containing 140 amino acids. Production of ACTIMMUNE is achieved by fermentation of a genetically engineered Escherichia coli bacterium containing the DNA which encodes for the recombinant protein. Purification of the product is achieved by conventional column chromatography. ACTIMMUNE is a highly purified sterile solution consisting of non-covalent dimers of two identical 16,465 Dalton monomers; with a specific activity of 20 million International Units/mg (2 × 10^6 International Units/0.5 mL) which is equivalent to 30 million units/mg.

ACTIMMUNE is a sterile, clear, colorless solution filled in a single-dose vial for subcutaneous injection. Each 0.5 mL of ACTIMMUNE contains: 100 mcg (2 million International Units) of interferon gamma-1b formulated in disodium succinate hexahydrate (0.37 mg), mannitol (20 mg), polysorbate 20 (0.05 mg), succinic acid (0.14 mg) and Sterile Water for Injection. Note that the above activity is expressed in International Units (1 million International Units/50 mcg). This is equivalent to what was previously expressed as units (1.5 million units/50 mcg).

12 CLINICAL PHARMACOLOGY

12.1 Mechanism of Action

Interferons bind to specific cell surface receptors and initiate a sequence of intracellular events that lead to the transcription of interferon-stimulated genes. The three major groups of interferons (alpha, beta, gamma) have partially overlapping biological activities that include immunoregulation such as increased resistance to microbial pathogens and inhibition of cell proliferation. Type 1 interferons (alpha and beta) bind to the alpha/ beta receptor. Interferon gamma binds to a different cell surface receptor and is classified as Type 2 interferon. Specific effects of interferon gamma include the enhancement of the oxidative metabolism of macrophages, antibody dependent cellular cytotoxicity (ADCC), activation of natural killer (NK) cells, and the expression of Fc receptors and major histocompatibility antigens.

CGD is an inherited disorder of leukocyte function caused by defects in the enzyme complex responsible for phagocyte superoxide generation. ACTIMMUNE does not increase phagocyte superoxide production even in treatment responders.

In SMO (an inherited disorder characterized by an osteoclast defect, leading to bone overgrowth, and by deficient phagocyte oxidative metabolism), a treatment-related enhancement of superoxide production by phagocytes was observed. ACTIMMUNE was found to enhance osteoclast function in vivo.

In both disorders, the exact mechanism(s) by which ACTIMMUNE has a treatment effect has not been established. Changes in superoxide levels during ACTIMMUNE therapy do not predict efficacy and should not be used to assess patient response to therapy.

12.3 Pharmacokinetics

Pharmacokinetic studies in patients with CGD have not been performed. The intravenous, intramuscular, and subcutaneous pharmacokinetics of ACTIMMUNE have been investigated in 24 healthy male subjects following single-dose administration of 100 mcg/m^2 (twice the recommended dose for CGD and SMO patients). ACTIMMUNE is rapidly cleared after intravenous administration (1.4 Liters/minute) and slowly absorbed after intramuscular or subcutaneous injection. After intramuscular or subcutaneous injection, the apparent fraction of dose absorbed was greater than 89%. The mean elimination half-life after intravenous administration of 100 mcg/m^2 in healthy male subjects was 38 minutes. The mean elimination half-lives for intramuscular and subcutaneous dosing with 100 mcg/m^2 were 2.9 and 5.9 hours, respectively. Peak plasma concentrations, determined by ELISA, occurred approximately 4 hours (1.5 ng/mL) after intramuscular dosing and 7 hours (0.6 ng/mL) after subcutaneous dosing. Multiple dose subcutaneous pharmacokinetic studies were conducted in 38 healthy male subjects. There was no accumulation of ACTIMMUNE after 12 consecutive daily injections of 100 mcg/m^2.

Interferon gamma was not detected in the urine of healthy human volunteers following administration of 100 mcg/m^2 of ACTIMMUNE by the intravenous, intramuscular and subcutaneous routes. In vitro perfusion studies utilizing rabbit livers and kidneys demonstrate that these organs are capable of clearing interferon gamma from perfusate.

13 NONCLINICAL TOXICOLOGY

13.1 Carcinogenesis, Mutagenesis, Impairment of Fertility

Carcinogenesis: ACTIMMUNE has not been tested for its carcinogenic potential.

Mutagenesis: Ames tests using five different tester strains of bacteria with and without metabolic activation revealed no evidence of mutagenic potential. ACTIMMUNE was tested in a micronucleus assay for its ability to induce chromosomal damage in bone marrow cells of mice following two intravenous doses of 20 mg/kg. No evidence of chromosomal damage was noted.

Impairment of Fertility: Female cynomolgus monkeys treated with daily subcutaneous doses of 30 or 150 mcg/kg ACTIMMUNE (approximately 20 and 100 times the human dose) exhibited irregular menstrual cycles or absence of cyclicity during treatment. Similar findings were not observed in animals treated with 3 mcg/kg ACTIMMUNE.

Female mice receiving recombinant murine IFN-interferon gamma (rmuIFN-gamma) at 32 times the maximum recommended clinical dose of ACTIMMUNE for 4 weeks via intramuscular injection exhibited an increased incidence of atretic ovarian follicles.

Male cynomolgus monkeys treated intravenously for 4 weeks with 8 times the maximum recommended clinical dose of ACTIMMUNE exhibited decreased spermatogenesis. Male mice receiving rmuIFN-gamma at 32 times the maximum recommended clinical dose of ACTIMMUNE for 4 weeks via intramuscular injection exhibited decreased spermatogenesis. The impact of this finding on fertility is not known.

Male mice treated subcutaneously with rmuIFN-gamma from shortly after birth through puberty, with 280 times the maximum recommended clinical dose of ACTIMMUNE exhibited profound yet reversible decreases in sperm counts and fertility, and an increase in the number of abnormal sperm.

The clinical significance of these findings observed following treatment of mice with rmuIFN-gamma is uncertain.

14 CLINICAL STUDIES

14.1 Effects in Chronic Granulomatous Disease (CGD)

A randomized, double-blind, placebo-controlled trial of ACTIMMUNE (interferon gamma-1b) in patients with CGD, was performed to determine whether ACTIMMUNE administered subcutaneously on a three times weekly schedule could decrease the incidence of serious infectious episodes and improve existing infectious and inflammatory conditions in patients with CGD. One hundred twenty-eight eligible patients were enrolled in this trial including patients with different patterns of inheritance. Most patients received prophylactic antibiotics. Patients ranged in age from 1 to 44 years with the mean age being 14.6 years. The study was terminated early following demonstration of a highly statistically significant benefit of ACTIMMUNE therapy compared to placebo with respect to time to serious infection (p=0.0036), the primary endpoint of the investigation. Serious infection was defined as a clinical event requiring hospitalization and the use of parenteral antibiotics. The final analysis provided further support for the primary endpoint (p=0.0006). There was a 67 percent reduction in relative risk of serious infection in patients receiving ACTIMMUNE (n=63) compared to placebo (n=65). Additional supportive evidence of treatment benefit included a twofold reduction in the number of primary serious infections in the ACTIMMUNE group (30 on placebo versus 14 on ACTIMMUNE, p=0.002) and the total number and rate of serious infections including recurrent events (56 on placebo versus 20 on ACTIMMUNE, p=<0.0001). Moreover, the length of hospitalization for the treatment of all clinical events provided evidence highly supportive of an ACTIMMUNE treatment benefit. Placebo patients required three times as many inpatient hospitalization days for treatment of clinical events compared to patients receiving ACTIMMUNE (1493 versus 497 total days, p=0.02). An ACTIMMUNE treatment benefit with respect to time to serious infection was consistently demonstrated in all subgroup analyses according to stratification factors, including pattern of inheritance, use of prophylactic antibiotics, as well as age. There was a 67 percent reduction in relative risk of serious infection in patients receiving ACTIMMUNE compared to placebo across all groups. The beneficial effect of ACTIMMUNE therapy was observed throughout the entire study, in which the mean duration of ACTIMMUNE administration was 8.9 months/patient.

14.2 Effects in Severe, Malignant Osteopetrosis (SMO)

A controlled, randomized trial in patients with SMO was conducted with ACTIMMUNE administered subcutaneously three times weekly. Sixteen patients were randomized to receive either ACTIMMUNE plus calcitriol (n=11), or calcitriol alone (n=5). Patients ranged in age from 1 month to 8 years, mean 1.5 years. Treatment failure was considered to be disease progression as defined by 1) death, 2) significant reduction in hemoglobin or platelet counts, 3) a serious bacterial infection requiring antibiotics, or 4) a 50 dB decrease in hearing or progressive optic atrophy. The median time to disease progression was significantly delayed in the ACTIMMUNE plus calcitriol arm versus calcitriol alone. In the treatment arm, the median was not reached. Based on the observed data, however, the median time to progression in this arm was at least 165 days versus a median of 65 days in the calcitriol alone arm. In an analysis which combined data from a second study, 19 of 24 patients treated with ACTIMMUNE plus or minus calcitriol for at least 6 months had reduced trabecular bone volume compared to baseline.

16 HOW SUPPLIED/STORAGE AND HANDLING

16.1 How Supplied

ACTIMMUNE (interferon gamma-1b) is a sterile, clear, colorless solution filled in a single-dose vial for subcutaneous injection. Each vial permits the extraction of up to 0.5 mL of ACTIMMUNE with additional volume to facilitate solution withdrawal. Each 0.5 mL of ACTIMMUNE contains: 100 mcg (2 million International Units) of interferon gamma-1b.

NDC Number | Size
75987-111-10 | One vial
75987-111-11 | Cartons of 12 vials

16.2 Storage and Handling

Store vials in the refrigerator at 2 to 8 °C (36 °F – 46 °F). Do Not Freeze. Avoid excessive or vigorous agitation. Do Not Shake. An unused vial of ACTIMMUNE can be stored at room temperature up to 12 hours prior to use. Discard vials if not used within the 12 hour period. Do not return to the refrigerator.

17 PATIENT COUNSELING INFORMATION

Advise the patient and/or their parents or caregivers to read the FDA-approved patient labeling (Information for Patient/Caregiver).

- Inform patients and/or their parents or caregiver regarding the potential benefits and risks associated with treatment. If home use is determined to be desirable by the physician, instructions on appropriate use should be given, including review of the contents of the Information for Patient/ Caregiver. This information is intended to aid in the safe and effective use of the medication. It is not a disclosure of all possible adverse or intended effects.
- If home use is prescribed, a puncture resistant container for the disposal of used syringes and needles should be used by the patient and/or parents or caregivers. Instruct patients thoroughly on the importance of proper disposal and caution the patient and/or patient or caregiver against any reuse of needles and syringes. The full container should be disposed of according to the directions provided by the physician.
- Advise the patients and/or their parents or caregivers that the most common adverse reactions occurring with ACTIMMUNE therapy are "flu-like" or constitutional symptoms such as fever, headache, chills, myalgia or fatigue [see Adverse Reactions (6.1)] which may decrease in severity as treatment continues. Some of the "flu-like" symptoms may be minimized by bedtime administration of ACTIMMUNE. Acetaminophen may also be used to prevent or partially alleviate the fever and headache.
- Advise patients and/or their parents or caregivers that they may experience undesirable effects such as fatigue, convulsion, confusional state, disorientation or hallucination during treatment. Therefore, caution should be recommended when driving a car or operating machinery. If patients experience any of these events, they should avoid potentially hazardous tasks such as driving or operating machinery. This effect may be enhanced by alcohol.

Manufactured by:
Horizon Therapeutics Ireland DAC
Dublin, Ireland
U.S. License No. 2022

© 2025 Amgen Inc. All rights reserved.

1XXXXXX-V5

Information for the Patient/Caregiver ACTIMMUNE® (Interferon gamma-1b)

DO NOT ADMINISTER ACTIMMUNE UNTIL YOUR PHYSICIAN HAS THOROUGHLY TRAINED YOU IN THE PROPER TECHNIQUES.

ACTIMMUNE is supplied in single-dose vials. The unused portion of each vial should be disposed of as instructed by your physician. DO NOT SHAKE.

Your physician will tell you what size needle and syringe to use and also give you instructions on sterile technique. Keep all used syringes and needles out of the reach of children. Follow your physician's instructions on the safe disposal of used syringes and needles.

MEASURING THE DOSE

In measuring the correct dose for injection, be sure to check that the ACTIMMUNE solution is clear. If the solution is cloudy or hazy, do not inject it, but return the ACTIMMUNE vial to your pharmacist or prescribing physician.

1.
Wash your hands thoroughly with soap and water before preparing the medication. This helps prevent infection.

2.
Check the date on the ACTIMMUNE vial to be sure the drug has not expired.

3.
Remove the protective plastic cap and wipe the rubber stopper located on top of the ACTIMMUNE vial with an alcohol swab.

4.
Draw air into the syringe by pulling back on the plunger. The amount of air should be equal to the ACTIMMUNE dose.

5.
Remove and save the needle guard. Slowly insert the needle straight through the center of the rubber stopper into the ACTIMMUNE vial.

6.
Gently push the plunger to discharge the air into the vial.

7.
Turn the vial upside down with the syringe needle still in it and hold it in one hand. Be sure the tip of the needle is in the solution. Using your other hand slowly pull back on the plunger in a continuous motion until the correct amount of ACTIMMUNE solution is in the syringe. Each vial contains enough ACTIMMUNE for removal of up to 0.5 mL, with a small additional amount present for ease of withdrawal.

8.
Remove the needle from the ACTIMMUNE vial and replace the needle guard until time of administration or injection. Administration should be as soon after filling the syringe as possible; do not store ACTIMMUNE in the syringe.

SELECTING THE INJECTION SITE

Your doctor or nurse will teach you how to locate appropriate injection sites. It is very important that you rotate the site of an injection each time you give the medication. Even if you or your child develop a preference for one site – as often happens – you still should rotate the injection site.

Following are the injection sites most often recommended:

- Upper Arm

- Abdomen

- Thigh

GIVING THE MEDICATION

Your doctor or nurse will provide you with hands-on training on how to give an injection. Needles and syringes should be used only once to insure sterility of both the needle and the syringe. The following is a review of the steps involved in giving the medication:

1.
Cleanse the injection site with an alcohol-saturated cotton ball or cotton swab.

2.
Remove the needle guard from the syringe filled with the proper dose of solution and hold the syringe the way you would hold a pencil. Double check that the correct amount of ACTIMMUNE solution is in the syringe.

3.
Squeeze the skin between your fingers before and during the injection. Insert the needle into the skin at a 45° angle with a quick, firm motion. This hurts less than pushing the needle in slowly.

4.
After the needle is in, pull back very slightly with one hand on the plunger to see if blood comes into the syringe. This is to be sure that the needle has not entered a blood vessel. If blood does come into the syringe, do not inject the ACTIMMUNE solution. Withdraw the needle and insert at another location.

5.
If blood does not come into the syringe, slowly (within a few seconds) inject the solution by gently pushing the plunger until the syringe is empty.

6.
Withdraw the needle quickly, pulling it straight out, and apply pressure over the injection site with a dry gauze pad or cotton ball. A drop of blood may appear. Put a Band-Aid® on the injection site if desired.

7.
To prevent injury, safely dispose of all used needles and syringes after a single dose as instructed by your physician by following these simple steps:

- Place all used needles and syringes in a hard, plastic container with a screw-on cap, or a metal container with a plastic lid, such as a coffee can properly labeled as to content. If a metal container is used, cut a small hole in the plastic lid and tape the lid to the metal container. When the metal container is full, cover the hole with tape and throw it away. If a hard, plastic container is used, always screw the cap on tightly after each use. When the plastic container is full, tape around the cap and throw it away.
- Do not use glass or clear, plastic containers, or any container that will be recycled or returned to a store.
- Always store the container out of the reach of children.
- Please check with your doctor, nurse or pharmacist for other suggestions. There may be special state and local laws that they will discuss with you.

8.
Occasionally a problem may develop at the injection site. If you notice any of the following signs or symptoms, contact your doctor or nurse:

- A lump or swelling that doesn't go away
- Bruising that doesn't go away
- Any signs of infection or inflammation at an injection site (pus, persistent redness, surrounding skin that is hot to the touch, persistent pain after the injection)

STORAGE

ACTIMMUNE (Interferon gamma-1b) must be refrigerated immediately. Refrigerate at 36° to 46° Fahrenheit (2° to 8° Centigrade). DO NOT FREEZE.

ACTIMMUNE is supplied in single- dose vials. The unused portion of each vial should be disposed of according to state and local regulations as instructed by your physician. If you have any questions, contact your physician.

Manufactured by:
Horizon Therapeutics Ireland DAC
Dublin, Ireland

© 2025 Amgen Inc. All rights reserved.

December 2024

PRINCIPAL DISPLAY PANEL - 100 mcg Vial Carton

NDC 75987-111-11

ACTIMMUNE®
(Interferon gamma-1b)

100 mcg

Rx Only

12 single-dose vials

KEEP REFRIGERATED